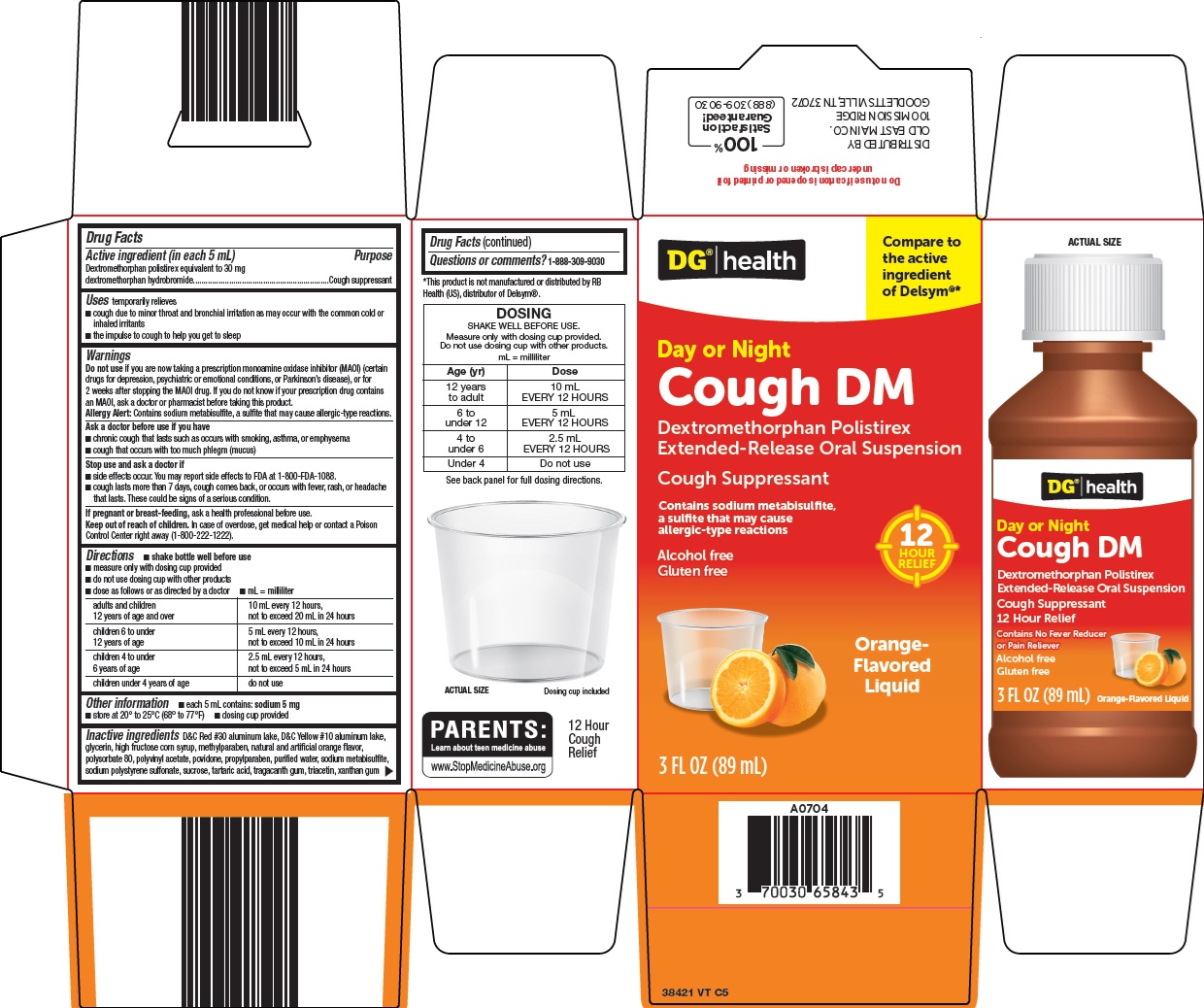 DRUG LABEL: DG Health Cough DM
NDC: 55910-384 | Form: SUSPENSION
Manufacturer: Dolgencorp Inc
Category: otc | Type: HUMAN OTC DRUG LABEL
Date: 20260121

ACTIVE INGREDIENTS: DEXTROMETHORPHAN HYDROBROMIDE 30 mg/5 mL
INACTIVE INGREDIENTS: POLISTIREX; D&C RED NO. 30 ALUMINUM LAKE; D&C YELLOW NO. 10 ALUMINUM LAKE; GLYCERIN; HIGH FRUCTOSE CORN SYRUP; METHYLPARABEN; POLYSORBATE 80; POLYVINYL ACETATE; POVIDONE, UNSPECIFIED; PROPYLPARABEN; WATER; SODIUM METABISULFITE; SODIUM POLYSTYRENE SULFONATE; SUCROSE; TARTARIC ACID; TRAGACANTH; TRIACETIN; XANTHAN GUM

Dolgencorp, LLC Cough DM Drug Facts

Active ingredient (in each 5 mL)

Dextromethorphan polistirex equivalent to 30 mg dextromethorphan hydrobromide

Purpose

Cough suppressant

Uses

temporarily relieves

- cough due to minor throat and bronchial irritation as may occur with the common cold or inhaled irritants
- the impulse to cough to help you get to sleep

Warnings

Do not use

if you are now taking a prescription monoamine oxidase inhibitor (MAOI) (certain drugs for depression, psychiatric or emotional conditions, or Parkinson’s disease), or for 2 weeks after stopping the MAOI drug. If you do not know if your prescription drug contains an MAOI, ask a doctor or pharmacist before taking this product.

Allergy Alert: Contains sodium metabisulfite, a sulfite that may cause allergic-type reactions.

Ask a doctor before use if you have

- chronic cough that lasts as occurs with smoking, asthma or emphysema
- cough that occurs with too much phlegm (mucus)

Stop use and ask a doctor if

- side effects occur. You may report side effects to FDA at 1-800-FDA-1088.
- cough lasts more than 7 days, cough comes back, or occurs with fever, rash or headache that lasts. These could be signs of a serious condition.

If pregnant or breast-feeding,

ask a health professional before use.

Keep out of reach of children.

In case of overdose, get medical help or contact a Poison Control Center right away (1-800-222-1222).

Directions

- shake bottle well before use
- measure only with dosing cup provided
- do not use dosing cup with other products
- dose as follows or as directed by doctor
- mL = milliliter

adults and children 12 years of age and over | 10 mL every 12 hours, not to exceed 20 mL in 24 hours
children 6 to under 12 years of age | 5 mL every 12 hours, not to exceed 10 mL in 24 hours
children 4 to under 6 years of age | 2.5 mL every 12 hours, not to exceed 5 mL in 24 hours
children under 4 years of age | do not use

Other information

- each 5 mL contains: sodium 5 mg
- store at 20° to 25°C (68° to 77°F)
- dosing cup provided

Inactive ingredients

D&C Red #30 aluminum lake, D&C Yellow #10 aluminum lake, glycerin, high fructose corn syrup, methylparaben, natural and artificial orange flavor, polysorbate 80, polyvinyl acetate, povidone, propylparaben, purified water, sodium metabisulfite, sodium polystyrene sulfonate, sucrose, tartaric acid, tragacanth gum, triacetin, xanthan gum

Questions or comments?

1-888-309-9030

Package/Label Principal Display Panel

DG® | health

Compare to the active ingredient of Delsym®

Day or Night

Cough DM

Dextromethorphan Polistirex

Extended-Release Oral Suspension

Cough Suppressant

Contains sodium metabisulfite, a sulfite that may cause allergic-type reactions

12 HOUR RELIEF

Alcohol free

Gluten free

Orange-Flavored Liquid

3 FL OZ (89 mL)